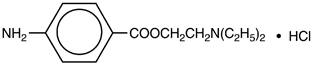 DRUG LABEL: Unknown
Manufacturer: Hospira, Inc.
Category: prescription | Type: Human prescription drug label
Date: 20070416

NOVOCAIN®
PROCAINE HYDROCHLORIDE INJECTION, USP

Local Anesthetic for Local Infiltration and Peripheral Nerve Block

THESE SOLUTIONS ARE NOT INTENDED FOR SPINAL OR EPIDURAL ANESTHESIA OR DENTAL USE

Rx only

DESCRIPTION

Procaine hydrochloride is benzoic acid, 4-amino-, 2-(diethylamino) ethyl ester, monohydrochloride, the ester of diethylaminoethanol and para-aminobenzoic acid, with the following structural formula:

It is a white crystalline, odorless powder that is freely soluble in water, but less soluble in alcohol and has a molecular weight of 272.78.

Composition of Available Solutions
Each mL contains | 1% Ampul | 1% Vial | 2% Vial
Procaine hydrochloride | 10 mg | 10 mg | 20 mg
Acetone sodium bisulfite | ≤ 1 mg | ≤ 2 mg | ≤ 2 mg
Chlorobutanol | – | ≤ 2.5 mg | ≤ 2.5 mg
[Acetone sodium bisulfite is added as an antioxidant in all products, and chlorobutanol is added as an antimicrobial preservative in the multiple-dose vials.]

The solutions are made isotonic with sodium chloride and the pH is adjusted between 3 and 5.5 with sodium hydroxide and/or hydrochloric acid.

Procaine hydrochloride is related chemically and pharmacologically to the ester-type local anesthetics. It contains an ester linkage between the aromatic nucleus and the amino group.

NOVOCAIN is available as sterile solutions in concentrations of 1% and 2% for injection via local infiltration and peripheral nerve block.

CLINICAL PHARMACOLOGY

Local anesthetics block the generation and the conduction of nerve impulses, presumably by increasing the threshold for electrical excitation in the nerve, by slowing the propagation of the nerve impulse, and by reducing the rate of rise of the action potential. In general, the progression of anesthesia is related to the diameter, myelination, and conduction velocity of affected nerve fibers. Clinically, the order of loss of nerve function is as follows: pain, temperature, touch, proprioception, and skeletal muscle tone. Procaine lacks topical anesthetic activity.

Systemic absorption of local anesthetics produces effects on the cardiovascular and central nervous systems. At blood concentrations achieved with normal therapeutic doses, changes in cardiac conduction, excitability, refractoriness, contractility, and peripheral vascular resistance are minimal. However, toxic blood concentrations depress cardiac conduction and excitability, which may lead to atrioventricular block and ultimately to cardiac arrest. In addition, myocardial contractility is depressed and peripheral vasodilation occurs, leading to decreased cardiac output and arterial blood pressure.

Following systemic absorption, local anesthetics can produce central nervous system stimulation, depression, or both. Apparent central stimulation is manifested as restlessness, tremors and shivering, progressing to convulsions, followed by depression, and coma progressing ultimately to respiratory arrest. However, the local anesthetics have a primary depressant effect on the medulla and on higher centers. The depressed stage may occur without a prior excited stage.

Pharmacokinetics:

The rate of systemic absorption of local anesthetics is dependent upon the total dose and concentration of drug administered, the route of administration, the vascularity of the administration site, and the presence or absence of epinephrine in the anesthetic solution. A dilute concentration of epinephrine (1:200,000 or 5 μg/mL) usually reduces the rate of absorption and plasma concentration of NOVOCAIN. It also will promote local hemostasis and increase the duration of anesthesia.

Onset of anesthesia with NOVOCAIN is rapid, the time of onset for sensory block ranging from about two to five minutes depending upon such factors as the anesthetic technique, the type of block, the concentration of the solution, and the individual patient. The degree of motor blockade produced is dependent on the concentration of the solution.

The duration of anesthesia also varies depending upon the technique and type of block, the concentration, and the individual. NOVOCAIN will normally provide anesthesia which is adequate for one hour.

Local anesthetics are bound to plasma proteins in varying degrees. Generally, the lower the plasma concentration of drug, the higher the percentage of drug bound to plasma.

Local anesthetics appear to cross the placenta by passive diffusion. The rate and degree of diffusion is governed by the degree of plasma protein binding, the degree of ionization, and the degree at lipid solubility. Fetal/maternal ratios of local anesthetics appear to be inversely related to the degree of plasma protein binding, because only the free, unbound drug is available for placental transfer. The extent of placental transfer is also determined by the degree of ionization and lipid solubility of the drug. Lipid, soluble nonionized drugs readily enter the fetalblood from the maternal circulation.

Depending upon the route of administration, local anesthetics are distributed to some extent to all body tissues, with high concentrations found in highly perfused organs such as the liver, lungs, heart, and brain.

Various pharmacokinetic parameters of the local anesthetics can be significantly altered by the presence of hepatic or renal disease, addition of epinephrine, factors affecting urinary pH, renal blood flow, the route of drug administration, and the age of the patient. The in vitro plasma half-life of NOVOCAIN in adults is 40 ± 9 seconds and in neonates 84 ± 30 seconds.

NOVOCAIN is readily absorbed following parenteral administration and is rapidly hydrolyzed by plasma cholinesterase to para-aminobenzoic acid and diethylaminoethanol.

The para-aminobenzoic acid metabolite inhibits the action of the sulfonamides. (See PRECAUTIONS.)

For NOVOCAIN, approximately 90% of the para-aminobenzoic acid metabolite and its conjugates and 33% of the diethylaminoethanol metabolite are recovered in the urine, while less than 2% of the administered dose is recovered unchanged in the urine.

INDICATIONS AND USAGE

NOVOCAIN is indicated for the production of local or regional analgesia and anesthesia by local infiltration and peripheral nerve block techniques.

The routes of administration and concentrations are: for local infiltration use 0.25% to 0.5% (via dilution) and for peripheral nerve blocks use 0.5% (via dilution), 1%, and 2%. (See DOSAGE AND ADMINISTRATION for additional information.)

Standard textbooks should be consulted to determine the accepted procedures and techniques for the administration of NOVOCAIN.

CONTRAINDICATIONS

NOVOCAIN is contraindicated in patients with a known hypersensitivity to procaine, drugs of a similar chemical configuration, or para-aminobenzoic acid or its derivatives.

It is also contraindicated in patients with a known hypersensitivity to other components of solutions of NOVOCAIN.

WARNINGS

Contains acetone sodium bisulfite, a sulfite that may cause allergic-type reactions including anaphylactic symptoms and life-threatening or less severe asthmatic episodes in certain susceptible people. The overall prevalence of sulfite sensitivity in the general population is unknown and probably low. Sulfite sensitivity is seen more frequently in asthmatic than in nonasthmatic people.

LOCAL ANESTHETICS SHOULD ONLY BE EMPLOYED BY CLINICIANS WHO ARE WELL VERSED IN DIAGNOSIS AND MANAGEMENT OF DOSE-RELATED TOXICITY AND OTHER ACUTE EMERGENCIES WHICH MIGHT ARISE FROM THE BLOCK TO BE EMPLOYED, AND THEN ONLY AFTER INSURING THE IMMEDIATE AVAILABILITY OF OXYGEN, OTHER RESUSCITATIVE DRUGS, CARDIOPULMONARY RESUSCITATIVE EQUIPMENT, AND THE PERSONNEL RESOURCES NEEDED FOR PROPER MANAGEMENT OF TOXIC REACTIONS AND RELATED EMERGENCIES. (See also ADVERSE REACTIONS and PRECAUTIONS.) DELAY IN PROPER MANAGEMENT OF DOSE-RELATED TOXICITY, UNDERVENTILATION FROM ANY CAUSE, AND/OR ALTERED SENSITIVITY MAY LEAD TO THE DEVELOPMENT OF ACIDOSIS, CARDIAC ARREST, AND, POSSIBLY, DEATH.

It is essential that aspiration for blood or cerebrospinal fluid, where applicable, be done prior to injecting any local anesthetic, both the original dose and all subsequent doses, to avoid intravascular or subarachnoid injection. However, a negative aspiration does not ensure against an intravascular or subarachnoid injection.

Reactions resulting in fatality have occurred on rare occasions with the use of local anesthetics, even in the absence of a history of hypersensitivity. Large doses of local anesthetics should not be used in patients with heartblock.

NOVOCAIN with epinephrine or other vasopressors should not be used concomitantly with ergot-type oxytocic drugs, because a severe persistent hypertension may occur. Likewise, solutions of NOVOCAIN containing a vasoconstrictor, such as epinephrine, should be used with extreme caution in patients receiving monoamine oxidase inhibitors (MAOI) or antidepressants of the triptyline or imipramine types, because severe prolonged hypertension or disturbances of cardiac rhythm may occur.

Local anesthetic procedures should be used with caution when there is inflammation and/or sepsis in the region of the proposed injection.

Mixing or the prior or intercurrent use of any local anesthetic with NOVOCAIN cannot be recommended because of insufficient data on the clinical use of such mixtures.

PRECAUTIONS

General:

The safety and effectiveness of local anesthetics depend on proper dosage, correct technique, adequate precautions, and readiness for emergencies. Resuscitative equipment, oxygen, and other resuscitative drugs should be available for immediate use. (See WARNINGS and ADVERSE REACTIONS.) During major regional nerve blocks, the patient should have IV fluids running via an indwelling catheter to assure a functioning intravenous pathway. The lowest dosage of local anesthetic that results in effective anesthesia should be used to avoid high plasma levels and serious adverse effects. Injections should be made slowly, with frequent aspirations before and during the injection to avoid intravascular injection. Current opinion favors fractional administration with constant attention to the patient, rather than rapid bolus injection. Syringe aspirations should also be performed before and during each supplemental injection in continuous (intermittent) catheter techniques. An intravascular injection is still possible even if aspirations for blood are negative.

Injection of repeated doses of local anesthetics may cause significant increases in plasma levels with each repeated dose due to slow accumulation of the drug or its metabolites or to slow metabolic degradation. Tolerance to elevated blood levels varies with the status of the patient. Debilitated, elderly patients and acutely ill patients should be given reduced doses commensurate with their age and physical status. Local anesthetics should also be used with caution in patients with severe disturbances of cardiac rhythm, shock, heartblock, or hypotension.

Careful and constant monitoring of cardiovascular and respiratory (adequacy of ventilation) vital signs and the patient’s state of consciousness should be performed after each local anesthetic injection. It should be kept in mind at such times that restlessness, anxiety, incoherent speech, light-headedness, numbness, and tingling of the mouth and lips, metallic taste, tinnitus, dizziness, blurred vision, tremors, twitching, depression, or drowsiness may be early warning signs of central nervous system toxicity.

Local anesthetic solutions containing a vasoconstrictor should be used cautiously and in carefully circumscribed quantities in areas of the body supplied by end arteries, or those areas having otherwise compromised blood supply such as digits, nose, external ear, penis. Patients with peripheral vascular disease and hypertensive vascular disease may exhibit an exaggerated vasoconstrictor response. Ischemic injury or necrosis may result.

NOVOCAIN should be used with caution in patients with known allergies and sensitivities. A thorough history of the patient’s prior experience with NOVOCAIN or other local anesthetics as well as concomitant or recent drug use should be taken. (See CONTRAINDICATIONS and WARNINGS.)

Because ester-type local anesthetics such as NOVOCAIN are hydrolyzed by plasma cholinesterase produced by the liver and excreted by the kidneys, these drugs, especially repeat doses, should be used cautiously in patients with hepatic disease. Because of their inability to metabolize local anesthetics normally, patients with severe hepatic disease are at a greater risk of developing toxic plasma concentrations. Local anesthetics should also be used with caution in patients with impaired cardiovascular function because they may be less able to compensate for functional changes associated with the prolongation of AV conduction produced by these drugs.

Serious dose-related cardiac arrhythmias may occur if preparations containing a vasoconstrictor such as epinephrine are employed in patients during or following the administration of potent inhalation anesthetics. In deciding whether to use these products concurrently in the same patient, the combined action of both agents upon the myocardium, the concentration and volume of vasoconstrictor used, and the time since injection, when applicable, should be taken into account.

Many drugs used during the conduction of anesthesia are considered potential triggering agents for familial malignant hyperthermia. Because it is not known whether ester-type local anesthetics may trigger this reaction and because the need for supplemental general anesthesia cannot be predicted in advance, it is suggested that a standard protocol for management should be available. Early unexplained signs of tachycardia, tachypnea, labile blood pressure, and metabolic acidosis may precede temperature elevation. Successful outcome is dependent on early diagnosis, prompt discontinuance of the suspect triggering agent(s), and institution of treatment, including oxygen therapy, indicated supportive measures, and dantrolene. (Consult dantrolene sodium intravenous package insert before using.)

Use in Head and Neck Area:

Small doses of local anesthetics injected into the head and neck area may produce adverse reactions similar to systemic toxicity seen with unintentional intravascular injections of larger doses. Confusion, convulsions, respiratory depression and/or respiratory arrest, and cardiovascular stimulation or depression have been reported.

These reactions may be due to intra-arterial injection of the local anesthetic with retrograde flow to the cerebral circulation. Patients receiving these blocks should have their circulation and respiration monitored and be constantly observed. Resuscitative equipment and personnel for treating adverse reactions should be immediately available. Dosage recommendations should not be exceeded.

Information for Patients:

When appropriate, patients should be informed, in advance, that they may experience temporary loss of sensation and motor activity following proper administration of regional anesthesia. Also, when appropriate, the physician should discuss other information including adverse reactions in the package insert.

Clinically Significant Drug Interactions:

The administration of local anesthetic solutions containing epinephrine or norepinephrine to patients receiving monoamine oxidase inhibitors or tricyclic antidepressants may produce severe, prolonged hypertension. Concurrent use of these agents should generally be avoided. In situations when concurrent therapy is necessary, careful patient monitoring is essential.

Concurrent administration of vasopressor drugs and of ergot-type oxytocic drugs may cause severe, persistent hypertension or cerebrovascular accidents.

Phenothiazines and butyrophenones may reduce or reverse the pressor effect of epinephrine.

The clinical observation has been made that despite adequate sulfonamide therapy, local infections have occurred in areas infiltrated with procaine hydrochloride prior to diagnostic punctures and drainage procedures. Therefore, NOVOCAIN should not be used in any condition in which a sulfonamide drug is being employed since para-aminobenzoic acid inhibits the action of the sulfonamide.

Carcinogenesis, Mutagenesis, and Impairment of Fertility:

Long-term studies in animals of most local anesthetics, including procaine hydrochloride, to evaluate the carcinogenic potential have not been conducted. Mutagenic potential or the effect on fertility have not been determined. There is no evidence from human data that NOVOCAIN may be carcinogenic, or mutagenic, or that it impairs fertility.

Pregnancy Category C:

Animal reproduction studies have not been conducted with NOVOCAIN. It is not known whether procaine can cause fetal harm when administered to a pregnant woman or can affect reproduction capacity. NOVOCAIN should be given to a pregnant woman only if clearly needed and the potential benefits outweigh the risk. This does not exclude the use of procaine hydrochloride at term for obstetrical anesthesia or analgesia. (See Labor and Delivery.)

Labor and Delivery:

Local anesthetics rapidly cross the placenta, and when used for paracervical or pudendal block anesthesia, can cause varying degrees of maternal, fetal, and neonatal toxicity. (See CLINICAL PHARMACOLOGY.) The incidence and degree of toxicity depend upon the procedure performed, the type and amount of drug used, and the technique of drug administration. Adverse reactions in the parturient, fetus, and neonate involve alterations of the central nervous system, peripheral vascular tone, and cardiac function.

Maternal hypotension has resulted from regional anesthesia. Local anesthetics produce vasodilation by blocking sympathetic nerves. Elevating the patient’s legs and positioning her on her left side will help prevent decreases in blood pressure. The fetal heart rate also should be monitored continuously and electronic fetal monitoring is highly advisable.

Paracervical or pudendal anesthesia may alter the forces at parturition through changes in uterine contractility or maternal expulsive efforts. In one study, paracervical block anesthesia was associated with a decrease in the mean duration of first stage labor and facilitation of cervical dilation. The use of obstetrical anesthesia may increase the need for forceps assistance.

The use of some local anesthetic drug products during labor and delivery may be followed by diminished muscle strength and tone for the first day or two of life. The long-term significance of these observations is unknown.

Fetal bradycardia which frequently follows paracervical block may be indicative of high fetal blood concentrations of procaine with resultant fetal acidosis. Fetal heart rate should be monitored prior to and during paracervical block. Added risk appears to be present in prematurity, toxemia of pregnancy, and fetal distress. The physician should weigh the considering paracervical block in these conditions. Careful adherence to recommended dosage is of the utmost importance in paracervical block. Failure to achieve adequate analgesia with these doses should arouse suspicion of intravascular or fetal injection.

Cases compatible with unintended fetal intracranial injection of local anesthetic solution have been reported following intended paracervical or pudendal block or both. Babies so affected present with unexplained neonatal depression at birth, which correlates with high local anesthetic serum levels, and usually manifest seizures within six hours. Prompt use of supportive measures combined with forced urinary excretion of the local anesthetic has been used successfully to manage this complication.

Case reports of maternal convulsions and cardiovascular collapse following use of some local anesthetics for paracervical block in early pregnancy (as anesthesia for elective abortion) suggest that systemic absorption under these circumstances may be rapid. The recommended maximum dose of the local anesthetic should not be exceeded. Injection should be made slowly and with frequent aspiration. Allow a five-minute interval between sides.

It is extremely important to avoid aortocaval compression by the gravid uterus during administration of regional block to parturients. To do this, the patient must be maintained in the left lateral decubitus position or a blanket roll or sandbag may be placed beneath the right hip and the gravid uterus displaced to the left.

Nursing Mothers:

It is not known whether local anesthetic drugs are excreted in human milk. Because many drugs are excreted in human milk, caution should be exercised when local anesthetics are administered to a nursing woman.

Pediatric Use:

(See DOSAGE AND ADMINISTRATION.)

ADVERSE REACTIONS

Reactions to procaine are characteristic of those associated with other ester-type local anesthetics. A major cause of adverse reactions to this group of drugs is excessive plasma levels which may be due to overdosage, rapid absorption, inadvertent intravascular injection, or slow metabolic degradation.

A small number of reactions may result from hypersensitivity, idiosyncrasy, or diminished tolerance to normal dosage.

Systemic:

The most commonly encountered acute adverse experiences which demand immediate countermeasures are related to the central nervous system and the cardiovascular system. These adverse experiences are generally dose related and due to high plasma levels which may result from overdosage, rapid absorption from the injection site, diminished tolerance, or from unintentional intravascular injection of the local anesthetic solution. In addition to systemic dose-related toxicity, unintentional subarachnoid injection of drug during the intended performance of nerve blocks near the vertebral column (especially in the head and neck region), may result in underventilation or apnea (“Total or High Spinal”). Factors influencing plasma protein binding, such as acidosis, systemic diseases which alter protein production, or competition of other drugs for protein binding sites may diminish individual tolerance.

Plasma cholinesterase deficiency may also account for diminished tolerance to ester-type local anesthetics.

Central Nervous System Reactions:

These are characterized by excitation and/or depression. Restlessness, anxiety, dizziness, tinnitus, blurred vision, or tremors may occur, possibly proceeding to convulsions. However, excitement may be transient or absent, with depression being the first manifestation of an adverse reaction. This may quickly be followed by drowsiness merging into unconsciousness and respiratory arrest.

The incidence of convulsions associated with the use of local anesthetics varies with the procedure used and the total dose administered.

Cardiovascular Reactions:

High doses or inadvertent intravascular injection may lead to high plasma levels and related depression of the myocardium, decreased cardiac output, heartblock, hypotension (or sometimes hypertension), bradycardia, ventricular arrhythmias, and cardiac arrest. (See WARNINGS, PRECAUTIONS, and OVERDOSAGE sections.)

Allergic:

Allergic-type reactions are rare and may occur as a result of sensitivity to the local anesthetic or to other formulation ingredients, such as the antimicrobial preservative chlorobutanol contained in multiple-dose vials. These reactions are characterized by signs such as urticaria, pruritus, erythema, angioneurotic edema (including laryngeal edema), tachycardia, sneezing, nausea, vomiting, dizziness, syncope, excessive sweating, elevated temperature, and, possibly, anaphylactoid-like symptomatology (including severe hypotension). Cross sensitivity among members of the ester-type local anesthetic group has been reported. The usefulness of screening for sensitivity has not been definitely established.

Neurologic:

The incidences of adverse neurologic reactions associated with the use of local anesthetics may be related to the total dose of local anesthetic administered, and are also dependent upon the particular drug used, the route of administration, and the physical status of the patient. Many of these effects may be related to local anesthetic techniques, with or without a contribution from the drug.

OVERDOSAGE

Acute emergencies from local anesthetics are generally related to high plasma levels encountered during therapeutic use of local anesthetics or to unintended subarachnoid injection of local anesthetic solution. (See ADVERSE REACTIONS, WARNINGS, and PRECAUTIONS.)

Management of Local Anesthetic Emergencies:

The first consideration is prevention, best accomplished by careful and constant monitoring of cardiovascular and respiratory vital signs, and the patient’s state of consciousness after each local anesthetic injection. At the first sign of change, oxygen should be administered.

The first step in the management of systemic toxic reactions, as well as underventilation or apnea due to unintentional subarachnoid injection of drug solution, consists of immediate attention to the establishment and maintenance of a patent airway, and effective assisted or controlled ventilation with 100% oxygen with a delivery system capable of permitting immediate positive airway pressure by mask. This may prevent convulsions if they have not already occurred.

If necessary, use drugs to control the convulsions. A 50 mg to 100 mg bolus IV injection of succinylcholine will paralyze the patient without depressing the central nervous or cardiovascular systems and facilitate ventilation. A bolus IV dose of 5 mg to 10 mg of diazepam or 50 mg to 100 mg of thiopental will permit ventilation and counteract central nervous system stimulation, but these drugs also depress central nervous system, respiratory and cardiac function, add to postictal depression, and may result in apnea. Intravenous barbiturates, anticonvulsant agents, or muscle relaxants should only be administered by those familiar with their use. Immediately after the institution of these ventilatory measures, the adequacy of the circulation should he evaluated. Supportive treatment of circulatory depression may require administration of intravenous fluids and, when appropriate, a vasopressor dictated by the clinical situation (such as ephedrine or epinephrine to enhance myocardial contractile force).

Endotracheal intubation, employing drugs and techniques familiar to the clinician, may be indicated, after initial administration of oxygen by mask, if difficulty is encountered in the maintenance of a patent airway or if prolonged ventilatory support (assisted or controlled) is indicated.

Recent clinical data from patients experiencing local anesthetic-induced convulsions demonstrated rapid development of hypoxia, hypercarbia, and acidosis within a minute of the onset of convulsions. These observations suggest that oxygen consumption and carbon dioxide production are greatly increased during local anesthetic convulsions, and emphasize the importance of immediate and effective ventilation with oxygen which may avoid cardiac arrest.

If not treated immediately, convulsions with simultaneous hypoxia, hypercarbia, and acidosis plus myocardial depression from the direct effects of the local anesthetic may result in cardiac arrhythmias, bradycardia, asystole, ventricular fibrillation, or cardiac arrest. Respiratory abnormalities, including apnea, may occur. Underventilation or apnea due to unintentional subarachnoid injection of local anesthetic solution may produce these same signs and also lead to cardiac arrest if ventilatory support is not instituted. If cardiac arrest should occur, standard cardiopulmonary resuscitative measures should be instituted and maintained for a prolonged period if necessary. Recovery has been reported after prolonged resuscitative efforts.

The supine position is dangerous in pregnant women at term because of aortocaval compression by the gravid uterus. Therefore, during treatment of systemic toxicity, maternal hypotension, or fetal bradycardia following regional block, the parturient should be maintained in the left lateral decubitus position if possible, or manual displacement of the uterus off the great vessels be accomplished.

The intravenous and subcutaneous and intraperitoneal LD50 of procaine hydrochloride in mice is 46 mg/kg to 80 mg/kg and 400 mg/kg and 200 mg/kg respectively.

DOSAGE AND ADMINISTRATION

The dose of any local anesthetic administered varies with the anesthetic procedure, the area to be anesthetized, the vascularity of the tissues, the number of neuronal segments to be blocked, the depth of anesthesia and degree of muscle relaxation required, the duration of anesthesia desired, individual tolerance, and the physical condition of the patient. The smallest dose and concentration required to produce the desired result should be administered. Dosages of NOVOCAIN should be reduced for elderly and debilitated patients and patients with cardiac and/or liver disease. The rapid injection of a large volume of local anesthetic solution should be avoided and fractional doses should be used when feasible.

For specific techniques and procedures, refer to standard textbooks.

For infiltration anesthesia, 0.25% or 0.5% solution; 350 mg to 600 mg is generally considered to be a single safe total dose. To prepare 60 mL of a 0.5% solution (5 mg/mL), dilute 30 mL of the 1% solution with 30 mL sodium chloride injection 0.9%. To prepare 60 mL of a 0.25% solution (2.5 mg/mL), dilute 15 mL of the 1% solution with 45 mL sodium chloride injection 0.9%. An anesthetic solution of 0.5 mL to 1 mL of epinephrine 1:1,000 per 100 mL may be added for vasoconstrictive effect (1:200,000 to 1:100,000). (See WARNINGS and PRECAUTIONS.)

For peripheral nerve block, 0.5% solution (up to 200 mL), 1% solution (up to 100 mL), or 2% solution (up to 50 mL). The use of the 2% solution should usually be limited to cases requiring a small volume of anesthetic solution (10 mL to 25 mL). An anesthetic solution of 0.5 mL to 1 mL of epinephrine 1:1,000 per 100 mL may be added for vasoconstrictive effect (1:200,000 to 1:100,000). (See WARNINGS and PRECAUTIONS.)

THE USUAL TOTAL DOSE DURING ONE TREATMENT SHOULD NOT EXCEED 1,000 MG.

This product should be inspected visually for particulate matter and discoloration prior to administration whenever solution and container permit. Do not use solutions if crystals, cloudiness, or discoloration is observed. Examine solution carefully before use. Reautoclaving increases likelihood of crystal formation. Solutions which are discolored or which contain particulate matter should not be administered.

Unused portions of solutions not containing preservatives should be discarded.

Pediatric Use:

In pediatric patients 15 mg/kg of a 0.5% solution for local infiltration is the maximum recommended dose.

HOW SUPPLIED

Single-dose containers and multiple-dose containers of NOVOCAIN may be sterilized by autoclaving at 15-pound pressure, 121°C (250°F) for 15 minutes. Do not use solutions if crystals, cloudiness, or discoloration is observed. Examine solution carefully before use. Reautoclaving increases likelihood of crystal formation. Do not administer solutions which are discolored or which contain particulate matter. Protect solutions from light.

Unused portions of solutions not containing preservatives, i.e., those supplied in ampuls, should be discarded following initial use.

THESE SOLUTIONS ARE NOT INTENDED FOR SPINAL OR EPIDURAL ANESTHESIA OR DENTAL USE.
List | Container | Concentration | Fill | Quantity
1808 | Uni-Amp® unit dose pak | 1 % | 2 mL | 25
1808 | Single-Dose Ampuls | 1 % | 6 mL | 50
1824 | Multiple-Dose Vials | 1 % | 30 mL | 1
1825 | Multiple-Dose Vials | 2 % | 30 mL | 1

November, 2004

©Hospira 2004 EN-0665 Printed in USA

HOSPIRA, INC., LAKE FOREST, IL 60045 USA